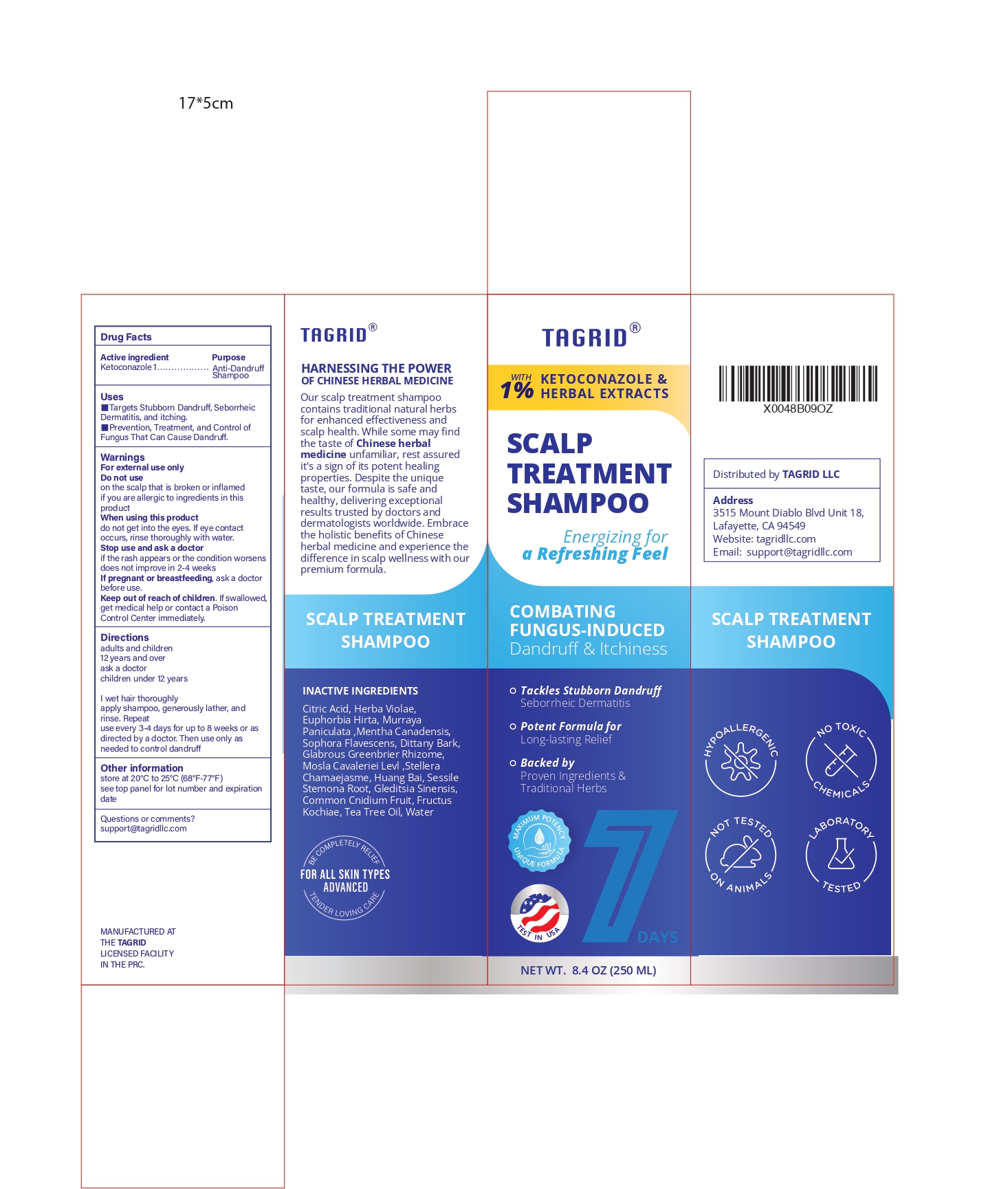 DRUG LABEL: 1% ketoconazole
NDC: 85384-0001 | Form: SHAMPOO
Manufacturer: TAGRID LLC
Category: otc | Type: HUMAN OTC DRUG LABEL
Date: 20250319

ACTIVE INGREDIENTS: KETOCONAZOLE 10 mg/1 mL
INACTIVE INGREDIENTS: PHELLODENDRON AMURENSE BARK; STEMONA SESSILIFOLIA ROOT; GLEDITSIA SINENSIS THORN; CNIDIUM MONNIERI FRUIT; MURRAYA PANICULATA ROOT BARK; DICTAMNUS DASYCARPUS ROOT BARK; STELLERA CHAMAEJASME WHOLE; MELALEUCA ALTERNIFOLIA (TEA TREE) LEAF OIL; CITRIC ACID; SMILAX GLABRA TUBER; WATER; SOPHORA FLAVESCENS ROOT; MENTHA CANADENSIS TOP OIL; EUPHORBIA HIRTA; MOSLA CAVALERIEI WHOLE; VIOLA YEZOENSIS WHOLE

Initial Drug Listing - Scalp Treatment Shampoo

ACTIVE INGREDIENT

ketoconazole 1%

PURPOSE

Anti Dandruff

INDICATIONS AND USAGE

- Targets Stubborn Dandruff, Seborrheic Dermatitis, and itching
- Prevention, Treatment, and control of fungus that can cause dandruff

WARNINGS

For external use only

DO NOT USE

on the scalp that is broken or inflamed if you are allergic to ingredients in this product

WHEN USING

do not get into the eyes. If eye contact occurs, rinse thoroughly with water.

STOP USE

If the rash appears or the condition worsens does not improve in 2-4 weeks.

ask a doctor before use

KEEP OUT OF REACH OF CHILDREN

If swallowed, get medical help or contact a Posion Control Center immediately

DOSAGE AND ADMINISTRATION

adults and children
12 years and over
• wet hair thoroughly
• apply shampoo, generously lather, rinse thoroughly. Repeat
• use every 3-4 days for up to 8 weeks or as directed by a doctor. Then use only as needed to control dandruff

Children under 12 years old • Ask a doctor

OTHER SAFETY INFORMATION

• store at 20°C to 25°C (68°F-77°F)
• see top panel for lot number and expiration date

QUESTIONS

Support@tagridllc.com

INACTIVE INGREDIENT

Citric Acid, Herba Violae, Euphorbia Hirta, Murraya Paniculata ,Mentha Canadensis, Sophora Flavescens, Dittany Bark, Glabrous Greenbrier Rhizome, Mosla Cavaleriei Levl ,Stellera Chamaejasme, Huang Bai, Sessile Stemona Root, Gleditsia Sinensis, Common Cnidium Fruit, Fructus Kochiae, Tea Tree Oil, Water